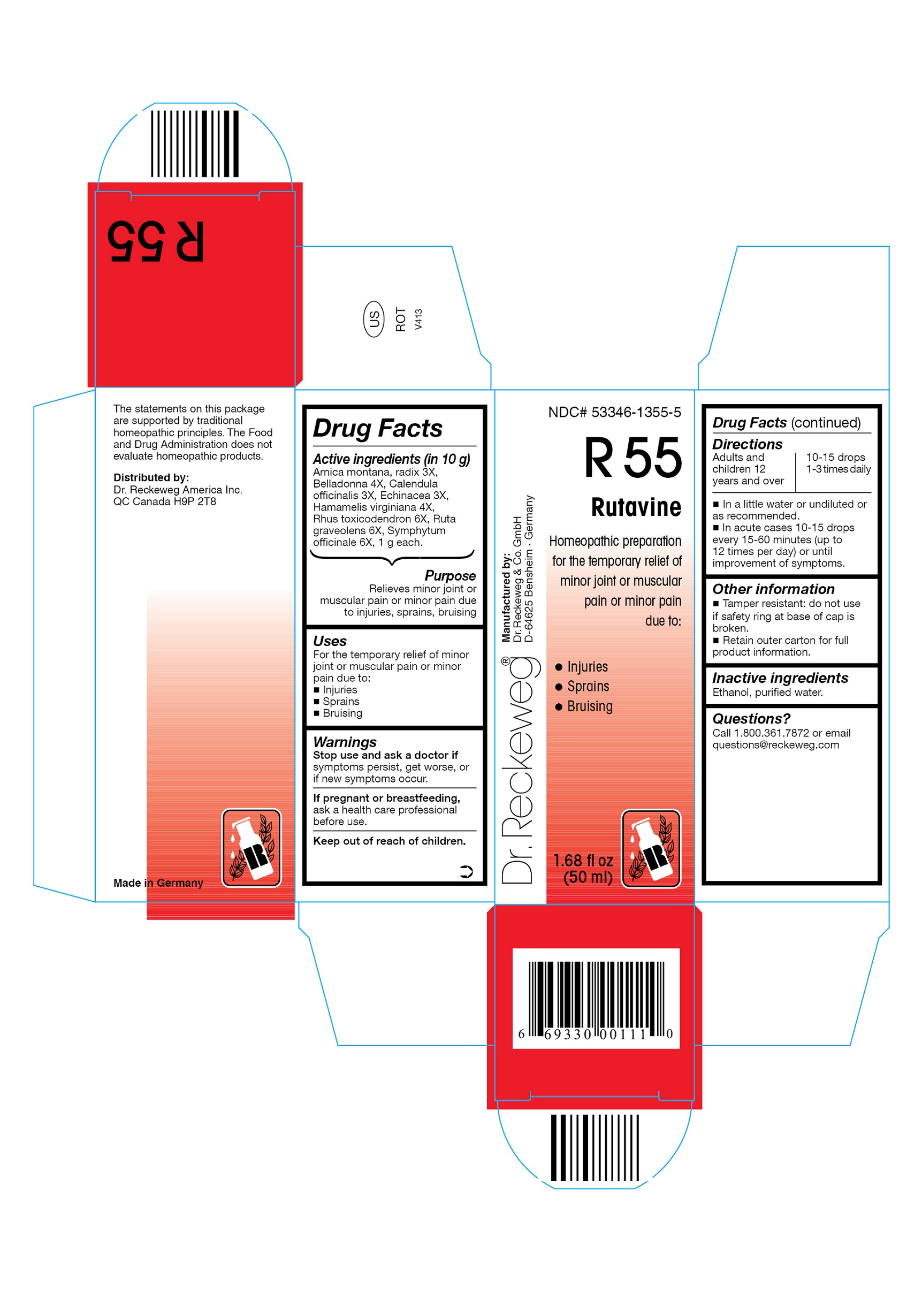 DRUG LABEL: DR. RECKEWEG R55 Rutavine
NDC: 53346-1355 | Form: LIQUID
Manufacturer: PHARMAZEUTISCHE FABRIK DR. RECKEWEG & CO
Category: homeopathic | Type: HUMAN OTC DRUG LABEL
Date: 20130515

ACTIVE INGREDIENTS: ARNICA MONTANA ROOT 3 [hp_X]/50 mL; ATROPA BELLADONNA 4 [hp_X]/50 mL; CALENDULA OFFICINALIS FLOWERING TOP 3 [hp_X]/50 mL; ECHINACEA, UNSPECIFIED 3 [hp_X]/50 mL; HAMAMELIS VIRGINIANA ROOT BARK/STEM BARK  4 [hp_X]/50 mL; TOXICODENDRON PUBESCENS LEAF 6 [hp_X]/50 mL; RUTA GRAVEOLENS FLOWERING TOP 6 [hp_X]/50 mL; COMFREY ROOT 6 [hp_X]/50 mL
INACTIVE INGREDIENTS: ALCOHOL; WATER

DR. RECKEWEG R55 Rutavine

Active ingredients

Arnica montana, radix 3X, Belladonna 4X, Calendula officinalis 3X, Echinacea 3X, Hamamelis virginiana 4X, Rhus toxicodendron 6X, Ruta graveolens 6X, Symphytum officinale 6X,

1 g each in 10 g.

Purpose

Relieves minor joint or muscular pain or minor pain due to injuries, sprains, bruising

Uses

For the temporary relief of minor joint or muscular pain or minor pain due to:

- Injuries
- Sprains
- Bruising

Warnings

Stop use and ask a doctor if symptoms persist, get worse, or if new symptoms occur.

PREGNANCY OR BREAST FEEDING

If pregnant or breastfeeding, ask a health care professional before use.

Keep out of reach of children.

Directions

Adults and children ≥ 12 years 10-15 drops 1-3 times daily; acute cases:

10-15 drops every 15-60 minutes (up to 12 times per day) or until improvement of symptoms in a little water or undiluted or as recommended.

Other information

- Tamper resistant: do not use if safety ring at base of cap is broken.
- Retain outer carton for full product information.

Inactive ingredients

Ethanol, purified water.

Questions?

Call 1.800.361.7872 or email questions@reckeweg.com

PACKAGE LABEL

NDC# 53346-1355-5
Dr. Reckeweg R55 Rutavine
Homeopathic preparation for the temporary relief of minor joint or muscular pain or minor pain due to:

- Injuries
- Sprains
- Bruising

Manufactured by:
Dr. Reckeweg Co. GmbH
D-64625 Bensheim
Germany
1.68 fl oz
(50 ml)